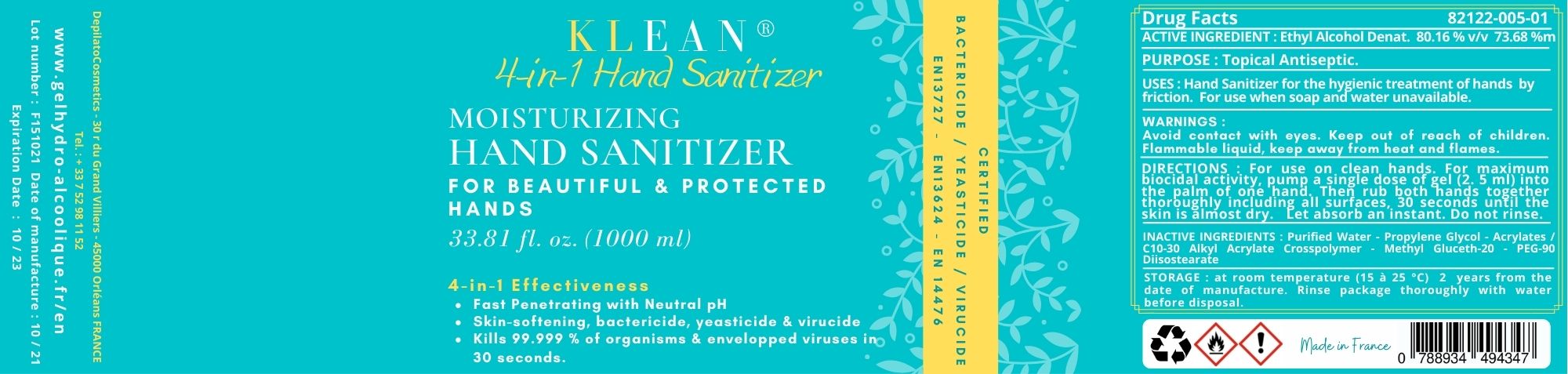 DRUG LABEL: KLEAN 4 IN 1 Hand Sanitizer
NDC: 82122-005 | Form: Gel
Manufacturer: DepilatoCosmetics SAS
Category: otc | Type: HUMAN OTC DRUG LABEL
Date: 20210830

ACTIVE INGREDIENTS: ALCOHOL 73.68 g/100 g
INACTIVE INGREDIENTS: CARBOMER INTERPOLYMER TYPE A (ALLYL SUCROSE CROSSLINKED) 0.35 g/100 g; PROPYLENE GLYCOL 0.8 g/100 g; WATER 24.68 g/100 g; METHYL GLUCETH-20 0.13 g/100 g; PEG-90 DIISOSTEARATE 0.25 g/100 g; AMINOMETHYLPROPANOL 0.11 g/100 g

KLEAN 4 IN 1 Hand Sanitizer

Active Ingredient(s)

Alcohol 80.16 % v/v. 73.68 % m/m Purpose: Antiseptic

Purpose

Topical Antiseptic

Use

Hand Sanitizer for the hygienic treatment of hands by
friction. For use when soap and water unavailable.

Warnings

For external use only. Flammable. Keep away from heat or flame

Do not use

- in children less than 2 months of age
- on open skin wounds

When using this product keep out of eyes, ears, and mouth. In case of contact with eyes, rinse eyes thoroughly with water.
Stop use and ask a doctor if irritation or rash occurs. These may be signs of a serious condition.
Keep out of reach of children. If swallowed, get medical help or contact a Poison Control Center right away.

Stop use and ask a doctor if irritation or rash occurs. These may be signs of a serious condition.

Keep out of reach of children. If swallowed, get medical help or contact a Poison Control Center right away.

Directions

- Place enough product on hands to cover all surfaces. Rub hands together until dry.
- Supervise children under 6 years of age when using this product to avoid swallowing.

Other information

- Store between 15-30C (59-86F)
- Avoid freezing and excessive heat above 40C (104F)

Inactive ingredients

glycerin, hydrogen peroxide, purified water USP

Package Label - Principal Display Panel

001 L (000 mL) NDC: 82122-005-01